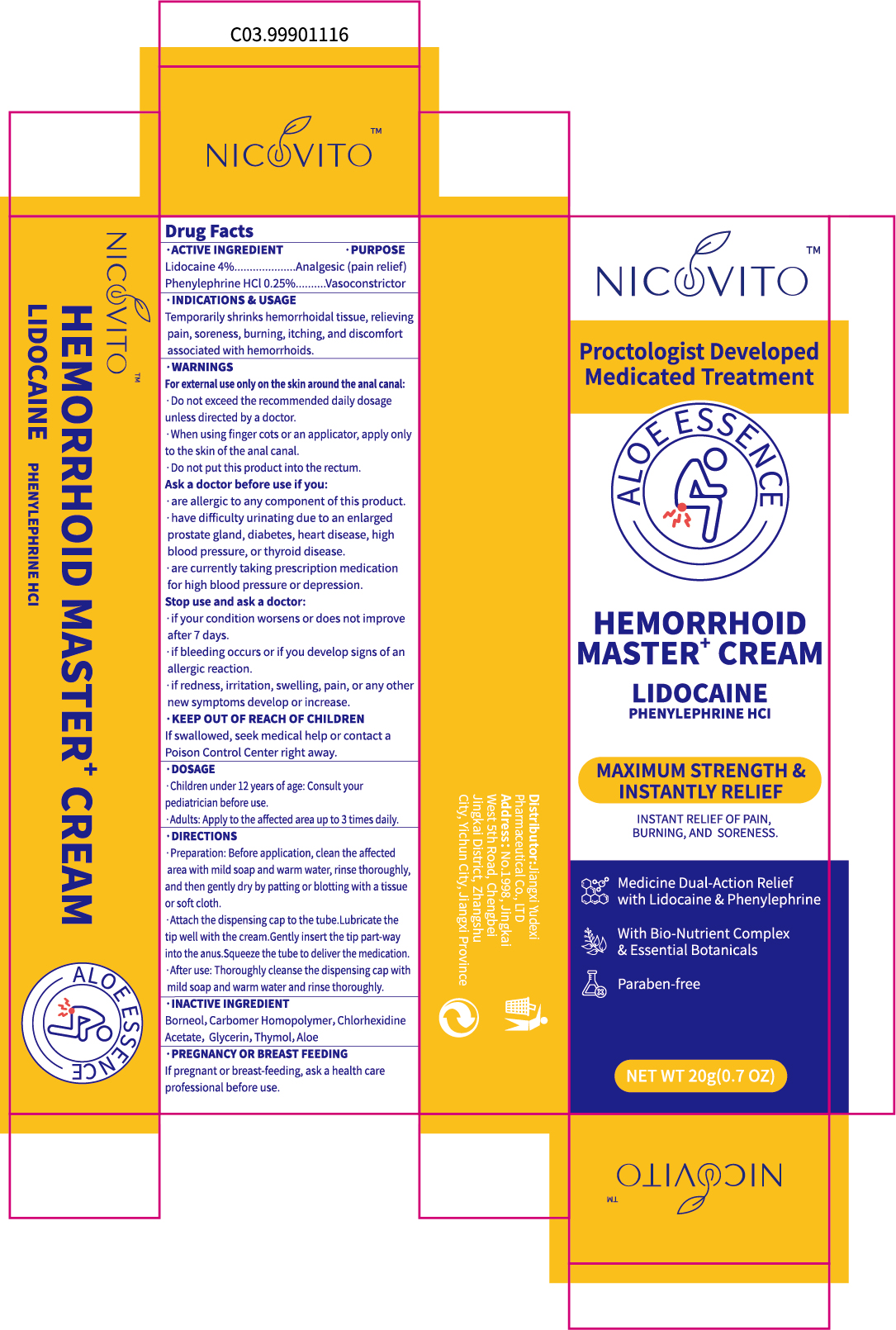 DRUG LABEL: NICOVITO  HEMORRHOID  MASTER
NDC: 85248-128 | Form: CREAM
Manufacturer: Jiangxi Yudexi Pharmaceutical Co., LTD
Category: otc | Type: HUMAN OTC DRUG LABEL
Date: 20260209

ACTIVE INGREDIENTS: LIDOCAINE 4 g/100 g; PHENYLEPHRINE HYDROCHLORIDE 0.25 g/100 g
INACTIVE INGREDIENTS: GLYCERIN; BORNEOL; CARBOMER HOMOPOLYMER, UNSPECIFIED TYPE; THYMOL; CHLORHEXIDINE ACETATE; ALOE

85248-128

Active Ingredient

Lidocaine 4% Phenylephrine HCl 0.25%

Purpose

Analgesic (pain relief) Vasoconstrictor

Use

Temporarily shrink hemorrhoidal tissue, relieving pain,soreness, burning, itching, and discomfort associated with hemorrhoids.

Warnings

For external use only on the skin around the anal canal:
·Do not exceed the recommended daily dosage unless directed by a doctor.
·When using finger cots or an applicator, apply only to the skin of the anal canal.
·Do not put this product into the rectum.

Do not use

·Do not put this product into the rectum.

When Using

·When using finger cots or an applicator, apply only to the skin of the anal canal.

Stop Use

·if your condition worsens or does not improve after 7 days.
.if bleeding occurs or if you develop signs of an allergic reaction.
·if redness, irritation, swelling, pain, or any other new symptoms develop or increase.

Ask Doctor

·are allergic to any component of this product.
· have difficulty urinating due to an enlarged prostate gland, diabetes, heart disease,
high blood pressure,or thyroid disease.
·are currently taking prescription medication for high blood pressure or depression.

Keep Oot Of Reach Of Children

If swallowed, seek medical help or contact a Poison Control Center right away.

Directions

Children under 12 years of age: consult your pediatrician before use. Adults: Apply to the affected area up to 3 times daily. ·Preparation: Before application, clean the affected area with mild soap and warm water, rinse thoroughly, and then gently dry by patting or blotting with a tissue or soft cloth.
·Attach the dispensing cap to the tube.Lubricate the tip well with the cream.Gently insert the tip part-way into the anus.Squeeze the tube to deliverthe medication. ·After use: Thoroughly cleanse the dispensing cap with mild soap and warm water
and rinse thoroughly.

Other information

If pregnant or breast-feeding, ask a health care professional before use.

Inactive ingredients

Borneol,Carbomer Homopolymer,Chlorhexidine Acetate ，Glycerin, Thymol, Aloe